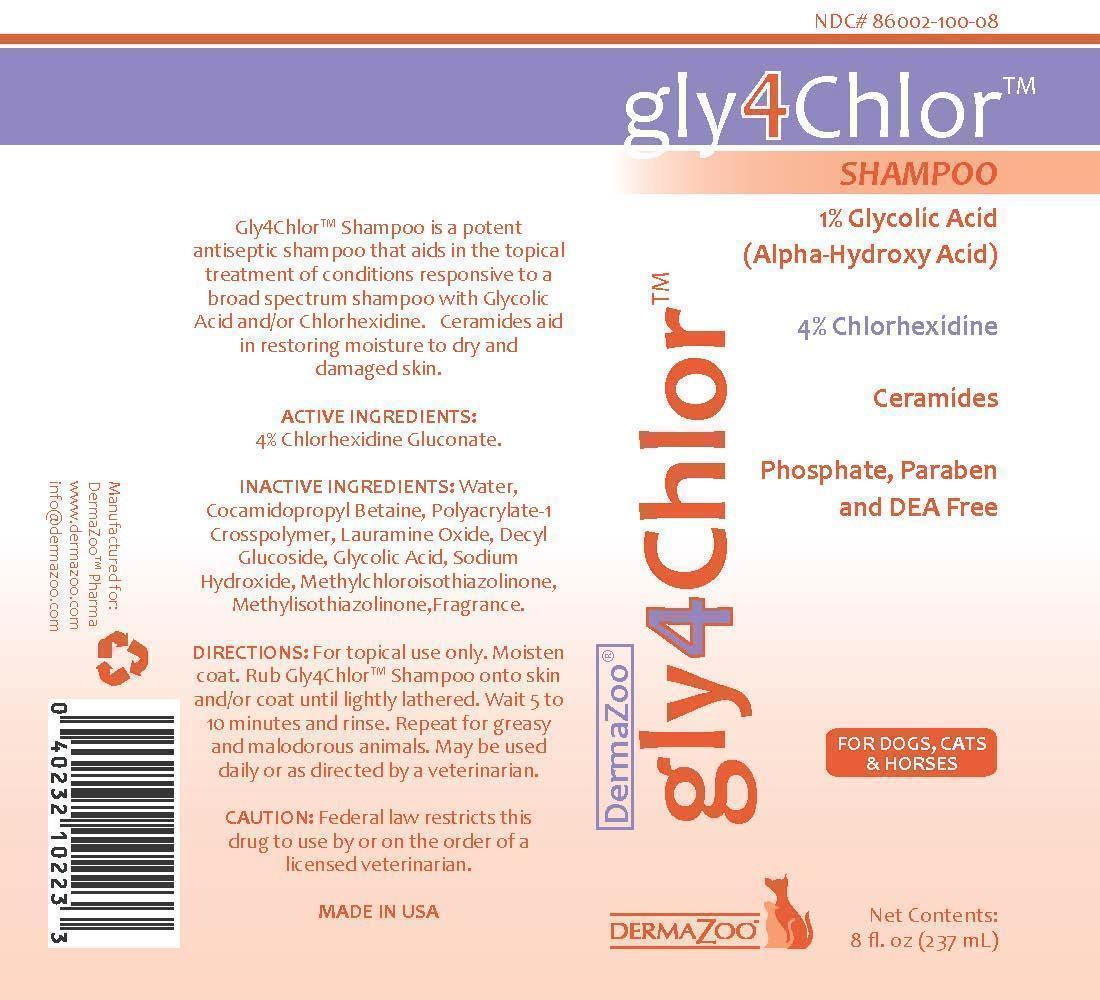 DRUG LABEL: gly4Chlor
NDC: 86002-100 | Form: SHAMPOO
Manufacturer: DermaZoo, LLC
Category: animal | Type: PRESCRIPTION ANIMAL DRUG LABEL
Date: 20240821

ACTIVE INGREDIENTS: CHLORHEXIDINE GLUCONATE 4 g/1000 mL
INACTIVE INGREDIENTS: WATER; COCAMIDOPROPYL BETAINE; POLYACRYLIC ACID (8000 MW); LAURAMINE OXIDE; DECYL GLUCOSIDE; GLYCOLIC ACID; SODIUM HYDROXIDE; METHYLCHLOROISOTHIAZOLINONE; METHYLISOTHIAZOLINONE

INDICATIONS AND USAGE

Gly4Chlor™ Shampoo is a potent antiseptic shampoo that aids in the topical treatment of conditions responsive to a broad spectrum shampoo with Glycolic Acid and/or Chlorhexidine. Ceramides aid in restoring moisture to dry and damaged skin.

DIRECTIONS: For topical use only. Moisten coat. Rub Gly4Chlor™ Shampoo onto skin and/or coat until lightly lathered. Wait 5 to 10 minutes and rinse. Repeat for greasy and malodorous animals. May be used daily or as directed by a veterinarian.

WARNINGS AND PRECAUTIONS

CAUTION: Federal law restricts this drug to use by or on the order of a licensed veterinarian.

DESCRIPTION

ACTIVE INGREDIENT: 4% Chlorhexidine Gluconate

INACTIVE INGREDIENTS: Water, Cocamidopropyl Betaine, Polyacrylate-1 Crosspolymer, Lauramine Oxide, Decyl Glucoside, Glycolic Acid, Sodium Hydroxide, Methylchloroisothiazolinone, Methylisothiazolinone, Fragrance.

Gly4Chlor™ Shampoo

1% Glycolic Acid (Alpha-Hydroxy Acid)

4% Chlorhexidine

Ceramides

Phospate, Paraben, and DEA Free

For Dogs, Cats & Horses

Net Contents: 8 fl. oz. (237 mL)

Made in USA

Manufactured for DermaZoo Pharma, www.dermazoo.com, info@dermazoo.com